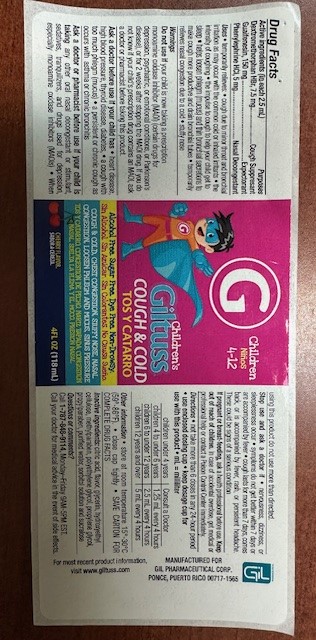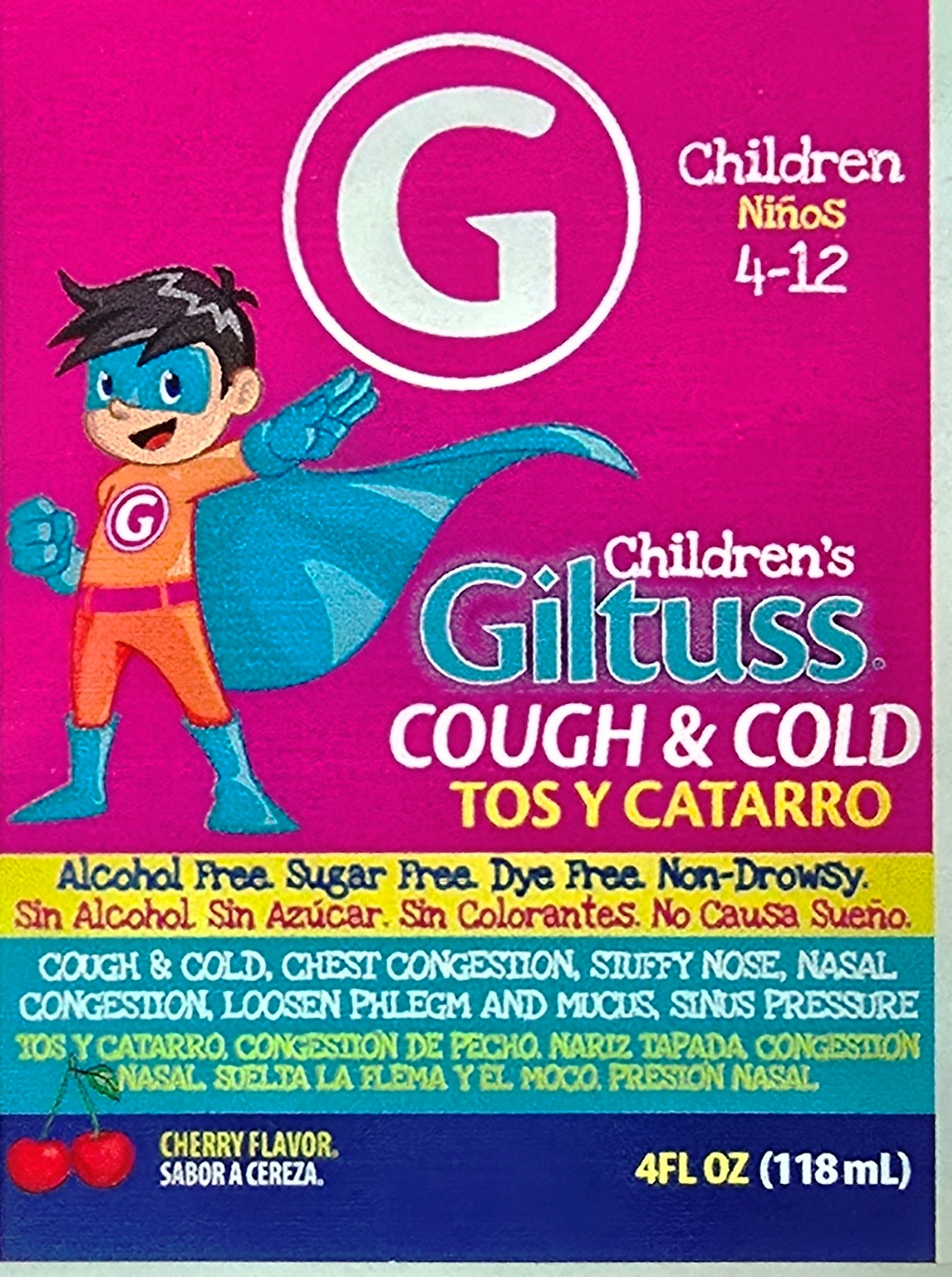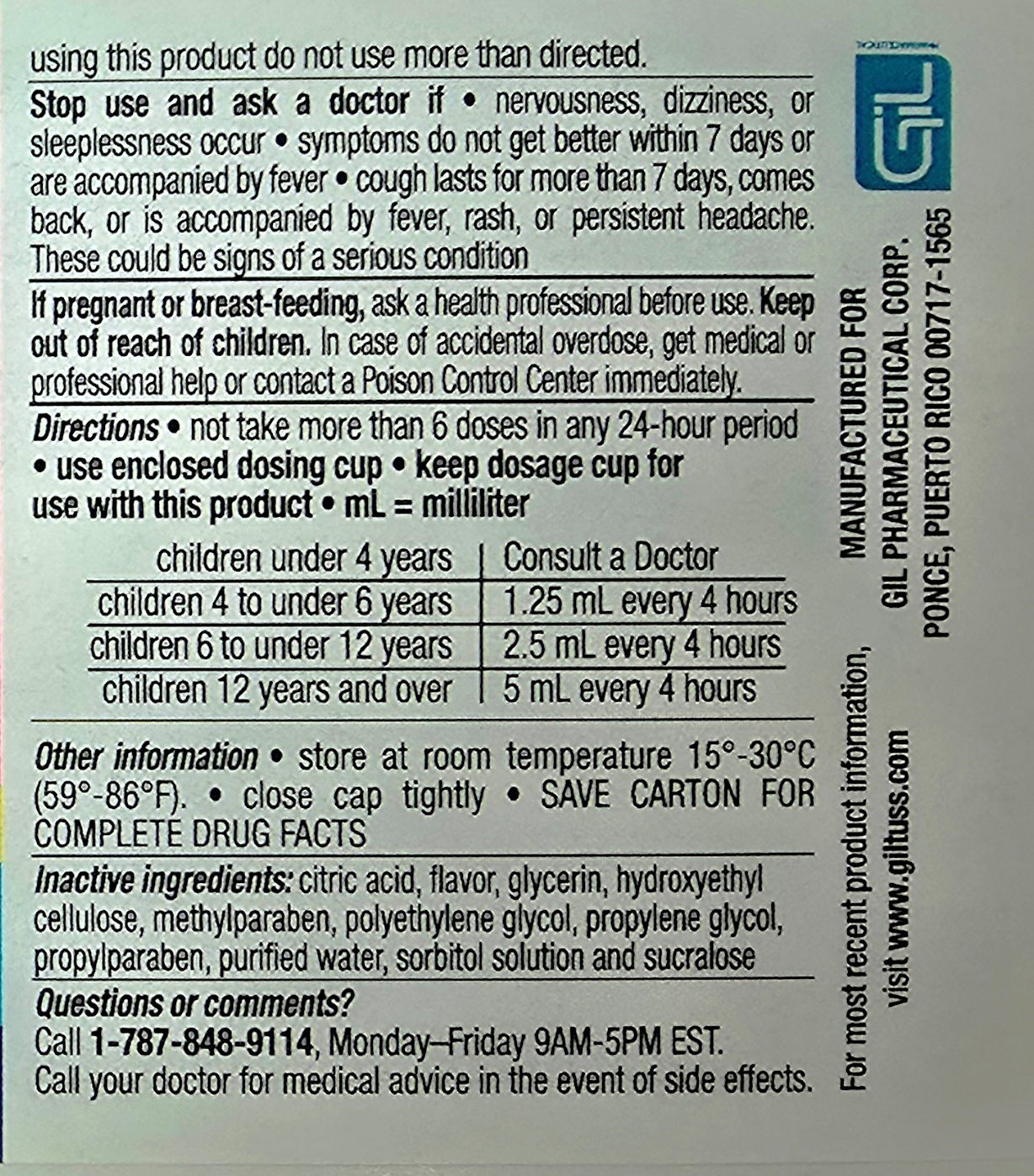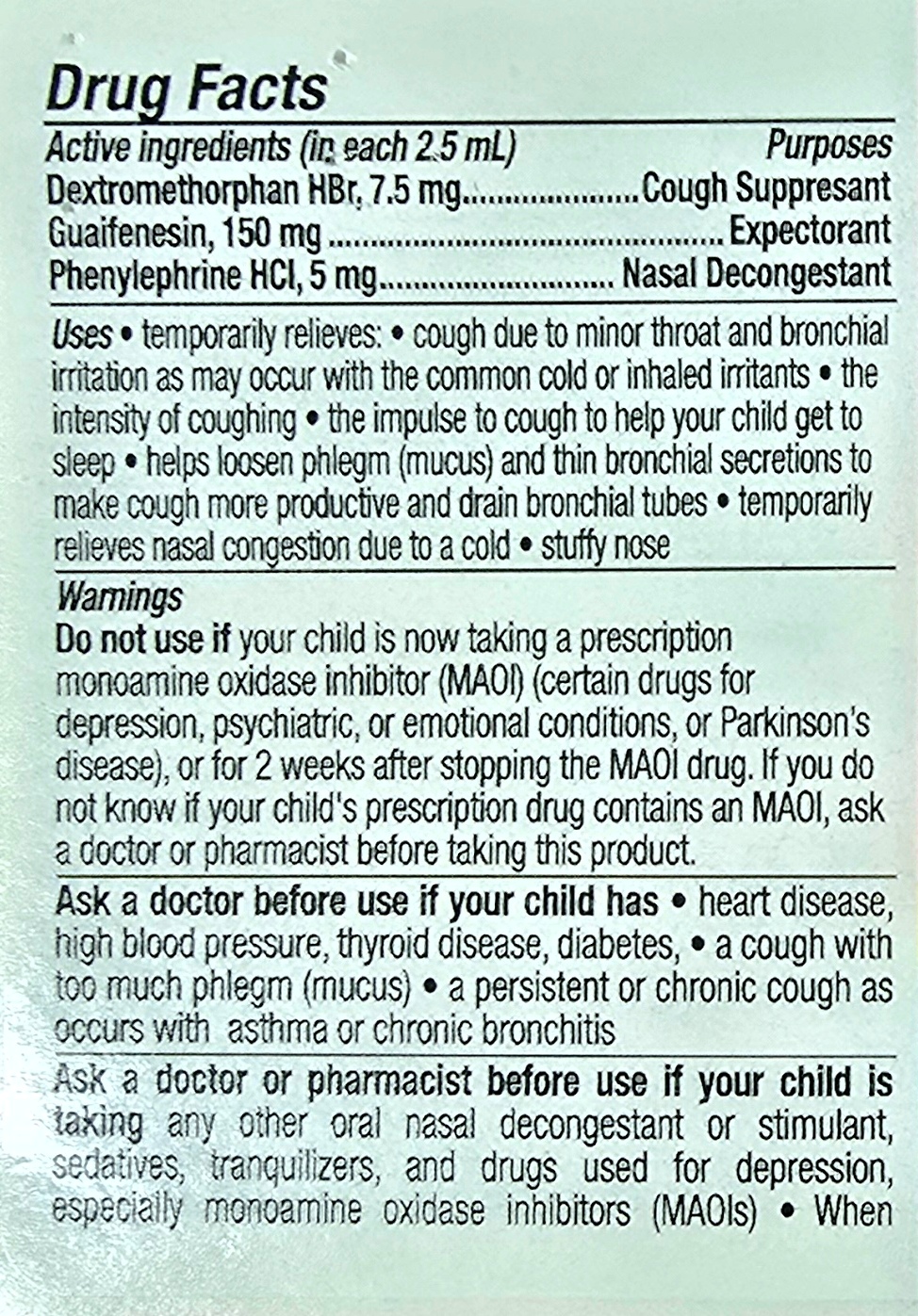 DRUG LABEL: Giltuss Childrens Cough and Cold
NDC: 65852-011 | Form: SOLUTION
Manufacturer: Dextrum Laboratories Inc.
Category: otc | Type: HUMAN OTC DRUG LABEL
Date: 20250917

ACTIVE INGREDIENTS: DEXTROMETHORPHAN HYDROBROMIDE 7.5 mg/2.5 mL; PHENYLEPHRINE HYDROCHLORIDE 5 mg/2.5 mL; GUAIFENESIN 150 mg/2.5 mL
INACTIVE INGREDIENTS: METHYLPARABEN; PROPYLENE GLYCOL; WATER; SUCRALOSE; GLYCERIN; PROPYLPARABEN; SORBITOL SOLUTION; CITRIC ACID; HYDROXYETHYL CELLULOSE, UNSPECIFIED; POLYETHYLENE GLYCOL, UNSPECIFIED

Children's Giltuss Cough & Cold

Drug Facts

Active Ingredients (in each 2.5 ml) Purposes

Dextrometorphan HBr, 7.5 mg ----------------------Cough suppresant

Guafenesin, 150 mg -----------------------------------Expectorant

Phenylepryne HCL, 5 mg -----------------------------Nasal Decongestant

Use section

Uses * temporary relieves* cough due to minor throat and bronchial irritation as may occur with the common cold or inhaled irritants*

the intensity of coughing**the impulse to cough to help your child get to sleep* helps loosen phlegm (mucus) and thin bronchial secretions to make cough more productive and drain bronchial tubes*temporary relieves nasal congestion due to a cold*stuffy nose

Warnings

Donot use if your child is now taking a prescription monoamine oxidase inhibitor (MAOI) (certain drugs for deppresion, psychiatric, or emotional conditions, or Parkinson's disease), or for 2 weeks after stopping the MAOI drug. If you do not know if your's child's prescription drug contains an MAOI, ask a doctor or pharmacist before taking this oroduct.

Ask a doctor before use if your child has *heart desease, high blood pressure, thryroid desease, diabetes* a cough with too much phlegm (mucus)* a persistent or chronic cough as occurs with asthma or chronic bronchitis

Ask a doctor or pharmacist before use if your child is taking any other nasal descongestant or stimulant, sedatives, tranquilizer, andndrugs used for depression, especially monoamine oxidase inhibitors (MAOIs)* When using this product do not use more than directed

Stop use and ask a Doctor if * nervousness,dizziness or sleeplesness occur* sympton do not get better within 7 days or are accompanied by fever* cough lasts for more than 7 days, comes back, or is accompanied by fever, rash, or persistent haedache . These could be signs of serious conditions.

PREGNANCY OR BREAST FEEDING

If pregnant or breast-feeding, ask a health professional before use. Keep out of reach of children. In case of accidental overdose , get medical or professional help or contact a Poisson Control Center inmediatly

Directions and other information

Directions* no take more than 6 doses in any 24 hours period * use enclosed dosing cup* keep dosage cup for use with this product* ml= mililiter

Children under 4 years ----Consult a doctor

children 4 to under 6 years------1.25 ml every 4 hours

children 6 to under 12 years-----2.5 ml every 4 hours

children 12 yeras and over -------5 ml every 4 hours

Other information

store at room temperature 15 - 30 0c* close cap tightly* save carton for complete drug facts

Questions section

Call 1-787-848-9114, Monday-Friday 9AM-5PM EST

Call your doctor for medical advice in the event of side efects

Active ingredients section

Active ingredients (in each 2.5 ml)

Dextrometorphan HBr, 7.5 mg

Guaifenesin,150 mg

Phenylephryne, 5 mg

Inactive Ingredients

Citric Acid, Flavor, Glycerin, Hydroxyethylcellulose, methylparaben, polyethylene glycol, propylene glycol, propylparaben, purified water, sorbitol solution, and sucralose

Keep out of reach of children

In case of accidental overdose , get medical or professional help or contact a Poison Control Center inmediatly

Indication and Usage section

no take more than 6 doses in any 24 hours period

use enclosed dosing cup* keep dosage cup for use with this product* ml= mililiter

Children under 4 years ----Consult a doctor

children 4 to under 6 years------1.25 ml every 4 hours

children 6 to under 12 years-----2.5 ml every 4 hours

children 12 yeras and over -------5 ml every 4 hours

Purpose sectiion

Cough Suppressant

Expectorant

Nasal descongestant

Principal panel

Childrens 4-12

Cough & Cold

Alcohol free

Sugar free

Dye free

Non -Drowsy

Cherry Flavor